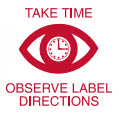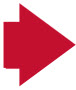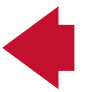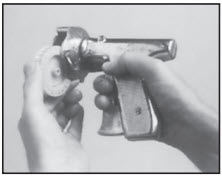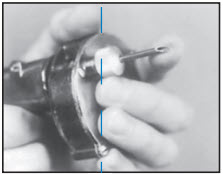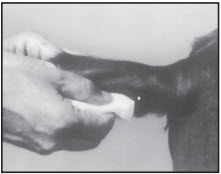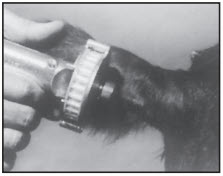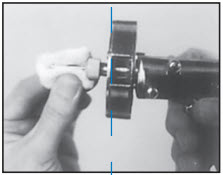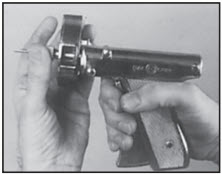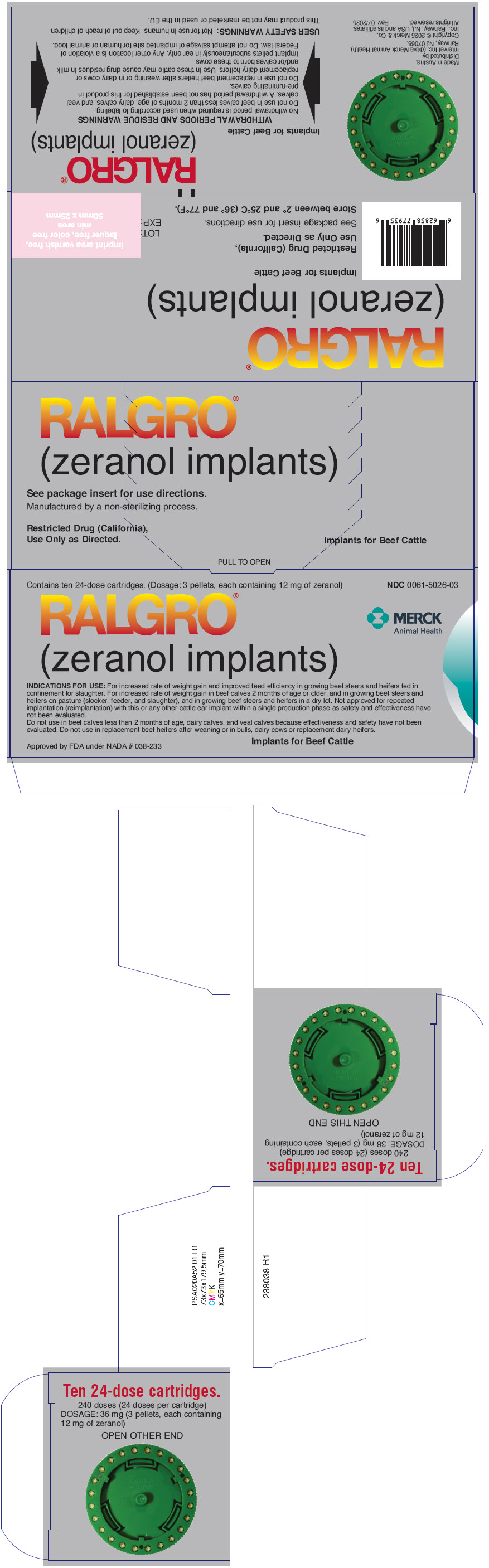 DRUG LABEL: RALGRO
NDC: 0061-5026 | Form: IMPLANT
Manufacturer: Merck Sharp & Dohme Corp.
Category: animal | Type: OTC ANIMAL DRUG LABEL
Date: 20251110

ACTIVE INGREDIENTS: ZERANOL 12 mg/1 1

RALGRO®
(zeranol implants)
IMPLANTS
IN
CARTRIDGES
FOR
BEEF CATTLE

RALGRO® (zeranol implants) provide 36 mg of zeranol per implant (three 12-mg pellets per implant).

INDICATIONS AND USAGE

INDICATIONS FOR USE: For increased rate of weight gain and improved feed efficiency in growing beef steers and heifers fed in confinement for slaughter. For increased rate of weight gain in beef calves 2 months of age or older, and in growing beef steers and heifers on pasture (stocker, feeder, and slaughter), and in growing beef steers and heifers in a dry lot. Not approved for repeated implantation (reimplantation) with this or any other cattle ear implant within a single production phase as safety and effectiveness have not been evaluated.

Do not use in beef calves less than 2 months of age, dairy calves, and veal calves because effectiveness and safety have not been evaluated.

Do not use in replacement beef heifers after weaning or in bulls, dairy cows or replacement dairy heifers.

WITHDRAWAL PERIODS AND RESIDUE WARNINGS
No withdrawal period is required when used according to labeling.
Do not use in beef calves less than 2 months of age, dairy calves, and veal calves. A withdrawal period has
not been established for this product in pre-ruminating calves.
Do not use in replacement beef heifers after weaning or in dairy cows or replacement dairy heifers. Use in
these cattle may cause drug residues in milk and/or calves born to these cows.
Implant pellets subcutaneously in ear only. Any other location is a violation of Federal law. Do not attempt
salvage of implanted site for human or animal food.

Manufactured by a non-sterilizing process.

Restricted Drug (California), Use Only as Directed.

Approved by FDA under NADA # 038-233

Distributed by Intervet Inc. (d/b/a Merck Animal Health),
Rahway, NJ 07065.
Copyright © 2025 Merck & Co., Inc., Rahway, NJ, USA and its affiliates.
All rights reserved.
Rev. 07/2025

SAFE HANDLING WARNING

USER SAFETY WARNINGS: Not for use in humans. Keep out of reach of children.

ANIMAL SAFETY WARNINGS: Edema of the vulva and udder, teat elongation, rectal and vaginal prolapse, and signs of estrus may occur when heifers are implanted. Delayed testicular development may occur in young males. To avoid difficulty in castration, young males should be castrated at the time of implanting.

DOSAGE AND ADMINISTRATION

DIRECTIONS: A single pull of the RALOGUN® Pellet Injector trigger delivers one dose (36-mg provided as three 12-mg pellets per chamber).

STEP 1

Each chamber of the plastic RALGRO cartridge contains a full dose of RALGRO implants. Insert the cartridge in the magazine of the RALOGUN pellet injector with the hole in the axle of the cartridge pointed toward the handle of the RALOGUN pellet injector. After snapping into place, rotate cartridge clockwise to ensure proper seating, then check window at top to ensure that pellet chamber is aligned with plunger.

STEP 2

Always use sharp needle. A dull needle tears tissue and makes proper implanting difficult. Be sure that needle is fully seated in RALOGUN pellet injector. This ensures that pellets will be expelled from the needle as RALOGUN plunger is extended. Failure to set the needle could cause the last pellet to be left in the needle and not implanted.

STEP 3

After appropriately restraining the animal to allow access to the ear, cleanse the skin at the implant needle puncture site.

STEP 4

The implant site is subcutaneous, between the skin and cartilage on the back side of the ear and below the midline of the ear. The implant must not be placed closer to the head than the edge of the auricular cartilage ring farthest from the head. The location for insertion of the needle is a point toward the tip of the ear and at least a needle length away from the intended deposition site. Care should be taken to avoid injuring the major blood vessels or cartilage of the ear. Squeeze trigger of the RALOGUN pellet injector to deliver a full dose of RALGRO. Keep trigger depressed while withdrawing the needle to be sure that RALGRO implants stay in place.

STEP 5

Wipe needle with cotton or gauze moistened with alcohol or other suitable disinfectant. Do not dip needle in solution because solution clinging to inside of needle will cause plugging of needle.

STEP 6

Rotate cartridge in direction of arrow until a new dose is visible and centered in window. The RALOGUN pellet injector is now ready for next implantation.

STORAGE AND HANDLING

STORAGE: Store between 2° and 25° C (36° and 77° F).

QUESTIONS/COMMENTS? For a copy of the Safety Data Sheet or to report side effects, contact Merck Animal Health Technical Services at 1-800-211-3573.

For additional information about reporting side effects for animal drugs, contact FDA at 1-888-FDA-VETS or http://www.fda.gov/reportanimalae

Made in Austria

This product may not be marked or used in the EU.

Approved by FDA under NADA # 038-233

238036 R3

PRINCIPAL DISPLAY PANEL - 10 Cartridge Box

Contains ten 24-dose cartridges. (Dosage: 3 pellets, each containing 12 mg of zeranol)
NDC 0061-5026-03

RALGRO®
(zeranol implants)

MERCK
Animal Health

INDICATIONS FOR USE: For increased rate of weight gain and improved feed efficiency in growing beef steers and heifers fed in
confinement for slaughter. For increased rate of weight gain in beef calves 2 months of age or older, and in growing beef steers and
heifers on pasture (stocker, feeder, and slaughter), and in growing beef steers and heifers in a dry lot. Not approved for repeated
implantation (reimplantation) with this or any other cattle ear implant within a single production phase as safety and effectiveness have
not been evaluated.
Do not use in beef calves less than 2 months of age, dairy calves, and veal calves because effectiveness and safety have not been
evaluated. Do not use in replacement beef heifers after weaning or in bulls, dairy cows or replacement dairy heifers.

Approved by FDA under NADA # 038-233

Implants for Beef Cattle